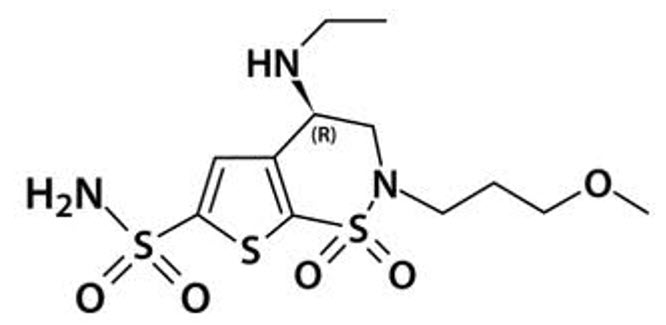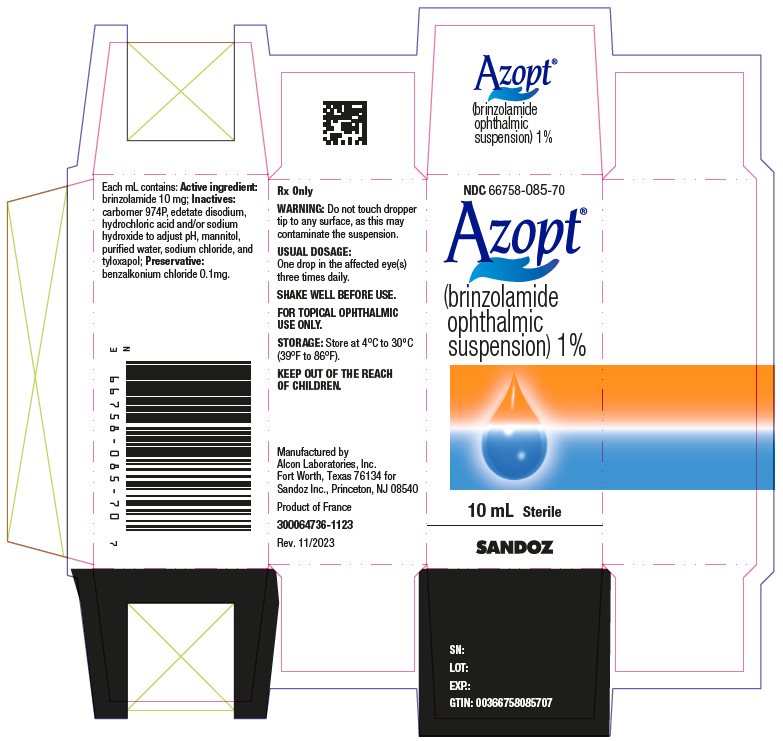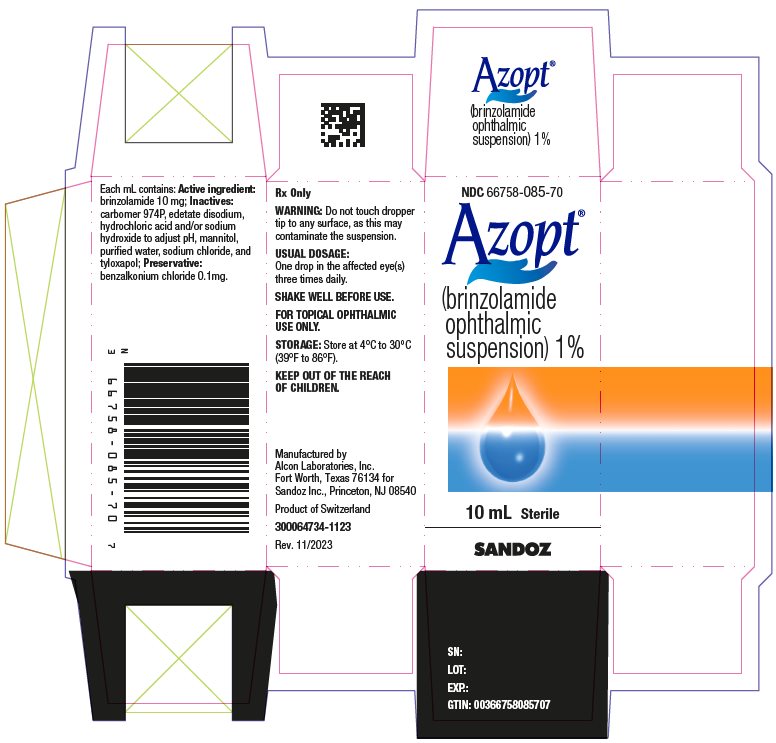 DRUG LABEL: Azopt
NDC: 66758-085 | Form: SUSPENSION/ DROPS
Manufacturer: Sandoz Inc
Category: prescription | Type: HUMAN PRESCRIPTION DRUG LABEL
Date: 20231124

ACTIVE INGREDIENTS: BRINZOLAMIDE 10 mg/1 mL
INACTIVE INGREDIENTS: MANNITOL; TYLOXAPOL; EDETATE DISODIUM; SODIUM CHLORIDE; HYDROCHLORIC ACID; SODIUM HYDROXIDE; WATER; BENZALKONIUM CHLORIDE; CARBOMER HOMOPOLYMER TYPE C (ALLYL PENTAERYTHRITOL CROSSLINKED)

HIGHLIGHTS OF PRESCRIBING INFORMATION

These highlights do not include all the information needed to use AZOPT safely and effectively. See full prescribing information for AZOPT.
AZOPT® (brinzolamide ophthalmic suspension) 1%, for topical ophthalmic use
Initial U.S. Approval: 1998

RECENT MAJOR CHANGES

Warnings and Precautions, Sulfonamide Hypersensitivity Reactions (5.1) 6/2023

1 INDICATIONS AND USAGE

AZOPT is a carbonic anhydrase inhibitor indicated for the treatment of elevated intraocular pressure (IOP) in patients with ocular hypertension or open-angle glaucoma. (1)

2 DOSAGE AND ADMINISTRATION

- Instill one drop in the affected eye(s) 3 times daily. (2)
- If more than one topical ophthalmic drug is being used, the drugs should be administered at least 10 minutes apart. (2)

3 DOSAGE FORMS AND STRENGTHS

Ophthalmic suspension containing brinzolamide 1% (10 mg/mL). (3)

4 CONTRAINDICATIONS

Hypersensitivity to any component of this product. (4)

5 WARNINGS AND PRECAUTIONS

- Sulfonamide hypersensitivity reactions. (5.1)
- Corneal edema may occur in patients with low endothelial cell counts. (5.2)

6 ADVERSE REACTIONS

Most common adverse reactions (incidence 5% to 10%) are blurred vision and bitter, sour, or unusual taste. (6.1)

To report SUSPECTED ADVERSE REACTIONS, contact Sandoz Inc. at 1-800-525-8747 or FDA at 1-800-FDA-1088 or www.fda.gov/medwatch.

7 DRUG INTERACTIONS

- There is a potential additive effect of the known systemic effects of carbonic anhydrase inhibition in patients receiving both oral and topical carbonic anhydrase inhibitors. (7.1)
- Rare instances of acid-base alterations have occurred with high-dose salicylate therapy. (7.2)

FULL PRESCRIBING INFORMATION

1 INDICATIONS AND USAGE

AZOPT is a carbonic anhydrase inhibitor indicated in the treatment of elevated intraocular pressure (IOP) in patients with ocular hypertension or open-angle glaucoma.

2 DOSAGE AND ADMINISTRATION

The recommended dose is one drop of AZOPT in the affected eye(s) 3 times daily. Shake well before use. AZOPT may be used concomitantly with other topical ophthalmic drug products to lower IOP. If more than one topical ophthalmic drug is being used, the drugs should be administered at least 10 minutes apart.

3 DOSAGE FORMS AND STRENGTHS

Ophthalmic suspension containing brinzolamide 1% (10 mg/mL).

4 CONTRAINDICATIONS

AZOPT is contraindicated in patients who are hypersensitive to any component of this product.

5 WARNINGS AND PRECAUTIONS

5.1 Sulfonamide Hypersensitivity Reactions

AZOPT is a sulfonamide and although administered topically, it is absorbed systemically. Therefore, the same types of adverse reactions that are attributable to sulfonamides may occur with topical administration of AZOPT. Fatalities have occurred, although rarely, due to severe reactions to sulfonamides, including Stevens-Johnson syndrome (SJS), toxic epidermal necrolysis (TEN), fulminant hepatic necrosis, agranulocytosis, aplastic anemia, and other blood dyscrasias. Sensitization may recur when a sulfonamide is readministered irrespective of the route of administration. If signs of serious reactions or hypersensitivity occur, discontinue the use of this preparation immediately.

5.2 Corneal Endothelium

Carbonic anhydrase activity has been observed in both the cytoplasm and around the plasma membranes of the corneal endothelium. There is an increased potential for developing corneal edema in patients with low endothelial cell counts. Caution should be used when prescribing AZOPT to this group of patients.

5.3 Severe Renal Impairment

AZOPT has not been studied in patients with severe renal impairment [creatinine clearance (CrCl) less than 30 mL/min]. Because AZOPT and its metabolite are excreted predominantly by the kidney, AZOPT is not recommended in such patients.

5.4 Acute Angle-Closure Glaucoma

The management of patients with acute angle-closure glaucoma requires therapeutic interventions in addition to ocular hypotensive agents. AZOPT has not been studied in patients with acute angle-closure glaucoma.

5.5 Risk of Contamination

Avoid allowing the tip of the dispensing container to contact the eye or surrounding structures or other surfaces, since the product can become contaminated by common bacteria known to cause ocular infections. Serious damage to the eye and subsequent loss of vision may result from using contaminated solutions.

5.6 Contact Lens Wear

The preservative in AZOPT, benzalkonium chloride, may be absorbed by soft contact lenses. Contact lenses should be removed during instillation of AZOPT, but may be reinserted 15 minutes after instillation.

6 ADVERSE REACTIONS

6.1 Clinical Trials Experience

Because clinical trials are conducted under widely varying conditions, adverse reaction rates observed in the clinical trials of a drug cannot be directly compared to the rates in the clinical trials of another drug and may not reflect the rates observed in practice.

In clinical studies of AZOPT, the most frequently reported adverse reactions reported in 5% to 10% of patients were blurred vision and bitter, sour, or unusual taste. Adverse reactions occurring in 1% to 5% of patients were blepharitis, dermatitis, dry eye, foreign body sensation, headache, hyperemia, ocular discharge, ocular discomfort, ocular keratitis, ocular pain, ocular pruritus, and rhinitis.

The following adverse reactions were reported at an incidence below 1%: allergic reactions, alopecia, chest pain, conjunctivitis, diarrhea, diplopia, dizziness, dry mouth, dyspnea, dyspepsia, eye fatigue, hypertonia, keratoconjunctivitis, keratopathy, kidney pain, lid margin crusting or sticky sensation, nausea, pharyngitis, tearing, and urticaria.

6.2 Postmarketing Experience

The following adverse reactions have been identified during postapproval use of brinzolamide containing products. Because these reactions are reported voluntarily from a population of uncertain size, it is not always possible to reliably estimate their frequency or establish a causal relationship to drug exposure.

Serious skin and subcutaneous tissue reactions, such as Stevens-Johnson syndrome (SJS) and Toxic epidermal necrolysis (TEN) may occur with the use of brinzolamide due to its sulfonamide component [see Warnings and Precautions (5.1)].

7 DRUG INTERACTIONS

7.1 Oral Carbonic Anhydrase Inhibitors

There is a potential for an additive effect on the known systemic effects of carbonic anhydrase inhibition in patients receiving an oral carbonic anhydrase inhibitor and AZOPT. The concomitant administration of AZOPT and oral carbonic anhydrase inhibitors is not recommended.

7.2 High-Dose Salicylate Therapy

Carbonic anhydrase inhibitors may produce acid-base and electrolyte alterations. These alterations were not reported in the clinical trials with brinzolamide. However, in patients treated with oral carbonic anhydrase inhibitors, rare instances of acid-base alterations have occurred with high-dose salicylate therapy. Therefore, the potential for such drug interactions should be considered in patients receiving AZOPT.

8 USE IN SPECIFIC POPULATIONS

8.1 Pregnancy

Risk Summary

There are no adequate and well-controlled studies in pregnant women to inform drug-associated risk.

In reproductive toxicity studies, brinzolamide administered orally to rats induced fetal toxicity at 375 times the recommended human ophthalmic dose (RHOD) based on mg/kg. In rabbits, no fetal toxicity was observed following oral administration (see Data).

The background risk of major birth defects and miscarriage for the indicated population is unknown; however, in the U.S. general population, the estimated background risk of major birth defects is 2% to 4%, and of miscarriage is 15% to 20%, of clinically recognized pregnancies.

Data

Animal Data

Embryo-fetal studies were conducted in pregnant rats administered 0, 2, 6, or 18 mg/kg/day brinzolamide by oral gavage on gestation days 6 to 17, to target the period of organogenesis. Decreased fetal body weight with reduced skeletal ossification were observed at 18 mg/kg/day (375 times the RHOD based on mg/kg). The no-observed-adverse-effect-level (NOAEL) for fetal toxicity was 6 mg/kg/day (125 times the RHOD). Decreased maternal weight gain was observed at 18 mg/kg/day. The NOAEL for maternal toxicity was 6 mg/kg/day (125 times the RHOD). Embryo-fetal studies were conducted in pregnant rabbits administered 0, 1, 3, or 6 mg/kg/day of brinzolamide by oral gavage on gestation days 6 to 18, to target the period of organogenesis. No treatment-related fetal effects were observed at any dose. The NOAEL for fetal toxicity was 6 mg/kg/day (125 times the RHOD based on mg/kg). Maternal weight loss during pregnancy was observed at 3 mg/kg/day (63 times the RHOD) and above. The NOAEL for maternal toxicity was 1 mg/kg/day (21 times the RHOD).

A peri-/postnatal study was conducted in rats administered brinzolamide by oral gavage from gestation day 16 through lactation day 20. Decreased pup body weight was observed at 15 mg/kg/day (313 times the RHOD based on mg/kg). The NOAEL for developmental toxicity was 5 mg/kg/day (104 times the RHOD). Following oral administration of ^14C-brinzolamide to pregnant rats, radioactivity was found to cross the placenta and was present in the fetal tissues and blood.

8.2 Lactation

Risk Summary

There are no data on the presence of brinzolamide in human milk, the effects on the breastfed infant, or the effects on milk production. Brinzolamide has been detected in the milk of lactating rats.

The developmental and health benefits of breastfeeding should be considered along with the mother’s clinical need for AZOPT and any potential adverse effects on the breastfed child from AZOPT.

8.4 Pediatric Use

A 3-month controlled clinical study was conducted in which AZOPT was dosed only twice a day in pediatric patients 4 weeks to 5 years of age. Patients were not required to discontinue their IOP-lowering medication(s) until initiation of monotherapy with AZOPT. IOP-lowering efficacy was not demonstrated in this study in which the mean decrease in elevated IOP was between 0 mmHg and 2 mmHg. Five out of 32 patients demonstrated an increase in corneal diameter of one millimeter.

8.5 Geriatric Use

No overall differences in safety or effectiveness have been observed between elderly and younger patients.

10 OVERDOSAGE

Although no human data are available, electrolyte imbalance, development of an acidotic state, and possible nervous system effects may occur following oral administration of an overdose. Serum electrolyte levels (particularly potassium) and blood pH levels should be monitored.

11 DESCRIPTION

AZOPT contains a carbonic anhydrase inhibitor formulated for multidose topical ophthalmic use. Brinzolamide is described chemically as: (R)-(+)-4-Ethylamino-2-(3-methoxypropyl)-3,4-dihydro-2H-thieno [3,2-e]-1,2-thiazine-6-sulfonamide-1,1- dioxide. Its empirical formula is C12H21N3O5S3, and its structural formula is:

Brinzolamide has a molecular weight of 383.5 g/mol and a melting point of about 131°C. It is a white powder, which is insoluble in water, very soluble in methanol and soluble in ethanol.

AZOPT is supplied as a sterile, aqueous suspension of brinzolamide which has been formulated to be readily suspended and slow settling, following shaking. It has a pH of approximately 7.5 and an osmolality of 300 mOsm/kg.

Each mL of AZOPT contains: Active ingredient: brinzolamide 10 mg; Inactives: carbomer 974P, edetate disodium, hydrochloric acid and/or sodium hydroxide to adjust pH, mannitol, purified water, sodium chloride, and tyloxapol; Preservative: benzalkonium chloride 0.1 mg.

12 CLINICAL PHARMACOLOGY

12.1 Mechanism of Action

Carbonic anhydrase is an enzyme found in many tissues of the body, including the eye. It catalyzes the reversible reaction involving the hydration of carbon dioxide and the dehydration of carbonic acid. In humans, carbonic anhydrase exists as a number of isoenzymes, the most active being carbonic anhydrase II, found primarily in red blood cells (RBCs), but also in other tissues. Inhibition of carbonic anhydrase in the ciliary processes of the eye decreases aqueous humor secretion, presumably by slowing the formation of bicarbonate ions with subsequent reduction in sodium and fluid transport. The result is a reduction in IOP.

AZOPT contains brinzolamide, an inhibitor of carbonic anhydrase II. Following topical ocular administration, brinzolamide inhibits aqueous humor formation and reduces elevated IOP. Elevated IOP is a major risk factor in the pathogenesis of optic nerve damage and glaucomatous visual field loss.

12.3 Pharmacokinetics

Following topical ocular administration, brinzolamide is absorbed into the systemic circulation. Due to its affinity for carbonic anhydrase II, brinzolamide distributes extensively into the RBCs and exhibits a long half-life in whole blood (approximately 111 days). In humans, the metabolite N-desethyl brinzolamide is formed, which also binds to carbonic anhydrase and accumulates in RBCs. This metabolite binds mainly to carbonic anhydrase I in the presence of brinzolamide. In plasma, both parent brinzolamide and N-desethyl brinzolamide concentrations are low and generally below assay quantitation limits (less than 10 ng/mL). Binding to plasma proteins is approximately 60%. Brinzolamide is eliminated predominantly in the urine as unchanged drug. N-Desethyl brinzolamide is also found in the urine along with lower concentrations of the N-desmethoxypropyl and O-desmethyl metabolites.

An oral pharmacokinetic study was conducted in which healthy volunteers received 1 mg capsules of brinzolamide twice per day for up to 32 weeks. This regimen approximates the amount of drug delivered by topical ocular administration of AZOPT dosed to both eyes 3 times per day and simulates systemic drug and metabolite concentrations similar to those achieved with long-term topical dosing. Red blood cell carbonic anhydrase activity was measured to assess the degree of systemic carbonic anhydrase inhibition. Brinzolamide saturation of RBC carbonic anhydrase II was achieved within 4 weeks (RBC concentrations of approximately 20 mcM). N-Desethyl brinzolamide accumulated in RBCs to steady-state within 20 to 28 weeks reaching concentrations ranging from 6 to 30 mcM. The inhibition of carbonic anhydrase II activity at steady-state was approximately 70% to 75%, which is below the degree of inhibition expected to have a pharmacological effect on renal function or respiration in healthy subjects.

13 NONCLINICAL TOXICOLOGY

13.1 Carcinogenesis, Mutagenesis, Impairment of Fertility

Carcinogenesis

Brinzolamide caused urinary bladder tumors in female mice at oral doses of 10 mg/kg/day and in male rats at oral doses of 8 mg/kg/day in 2-year studies. Brinzolamide was not carcinogenic in male mice or female rats dosed orally for up to 2 years. The carcinogenicity appears secondary to kidney and urinary bladder toxicity. These levels of exposure cannot be achieved with topical ophthalmic dosing in humans.

Mutagenesis

The following tests for mutagenic potential were negative: (1) in vivo mouse micronucleus assay; (2) in vivo sister chromatid exchange assay; and (3) Ames E. coli test. The in vitro mouse lymphoma forward mutation assay was negative in the absence of activation, but positive in the presence of microsomal activation.

Impairment of Fertility

In reproduction studies of brinzolamide in rats, there were no adverse effects on the fertility or reproductive capacity of males or females at doses up to 18 mg/kg/day (375 times the RHOD based on mg/kg).

14 CLINICAL STUDIES

In two, 3-month clinical studies, AZOPT dosed 3 times per day in patients with elevated IOP, produced significant reductions in IOPs (4 mmHg to 5 mmHg). These IOP reductions are equivalent to the reductions observed with TRUSOPT* (dorzolamide hydrochloride ophthalmic solution) 2% dosed 3 times per day in the same studies.

In 2 clinical studies in patients with elevated IOP, AZOPT was associated with less stinging and burning upon instillation than TRUSOPT* 2%.

16 HOW SUPPLIED/STORAGE AND HANDLING

AZOPT (brinzolamide ophthalmic suspension) 1% is supplied in plastic dispensers with a controlled dispensing-tip as follows:

10 mL NDC 66758-085-70

15 mL NDC 66758-085-85

Storage and Handling

Store AZOPT at 4°C to 30°C (39°F to 86°F). Shake well before use. After opening, AZOPT can be used until the expiration date on the bottle.

17 PATIENT COUNSELING INFORMATION

Sulfonamide Hypersensitivity Reactions

Advise patients that if serious or unusual ocular or systemic reactions or signs of hypersensitivity occur, they should discontinue the use of the product and consult their physician immediately [see Warnings and Precautions (5.1)].

Temporary Blurred Vision

Vision may be temporarily blurred following dosing with AZOPT. Advise patients to exercise care in operating machinery or driving a motor vehicle.

Avoiding Contamination of the Product

Instruct patients to avoid allowing the tip of the dispensing container to contact the eye or surrounding structures or other surfaces, since the product can become contaminated by common bacteria known to cause ocular infections. Serious damage to the eye and subsequent loss of vision may result from using contaminated solutions.

Intercurrent Ocular Conditions

Advise patients that if they have ocular surgery or develop an intercurrent ocular condition (e.g., trauma or infection), they should immediately seek their physician's advice concerning the continued use of the present multi-dose container.

Concomitant Topical Ocular Therapy

If more than one topical ophthalmic drug is being used, the drugs should be administered at least ten minutes apart.

Contact Lens Wear

The preservative in AZOPT, benzalkonium chloride, may be absorbed by soft contact lenses. Contact lenses should be removed during instillation of AZOPT, but may be reinserted 15 minutes after instillation.

*TRUSOPT is a registered trademark of Merck & Co., Inc.

Manufactured by

Alcon Laboratories, Inc.

Fort Worth, Texas 76134 for

Sandoz Inc., Princeton, NJ 08540

300064739-1123

PACKAGE/LABEL PRINCIPAL DISPLAY PANEL

NDC 66758-085-70

Azopt®

(brinzolamide

ophthalmic

suspension) 1%

10 mL Sterile

Sandoz

PRINCIPAL DISPLAY PANEL

NDC 66758-085-70

Azopt®

(brinzolamide
ophthalmic
suspension) 1%

10 mL Sterile

Sandoz